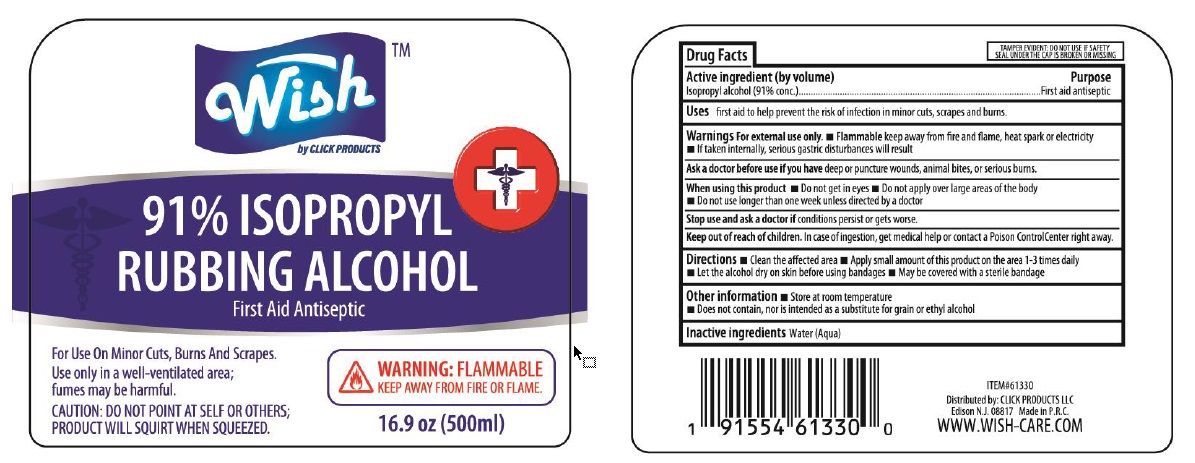 DRUG LABEL: Wish
NDC: 71611-055 | Form: SOLUTION
Manufacturer: CLICK PRODUCTS LLC
Category: otc | Type: HUMAN OTC DRUG LABEL
Date: 20200907

ACTIVE INGREDIENTS: ISOPROPYL ALCOHOL 91 mL/100 mL
INACTIVE INGREDIENTS: WATER

WISH- isopropyl alcohol solution

Active Ingredient

Isopropyl alcohol (91% conc.)

Purpose

First aid antiseptic

Use

First aid to help prevent the risk of infection in minor cuts, scrapes and burns

Warnings

Flammable keep away from fire and flame, heat spark or electricity.
If taken internally, serious gastric disturbances will result.

Ask a doctor before use if you have deep or puncture wounds, animal bites, or serious burns.

When using this product

- Do not get in eyes
- Do not apply over large areas of the body
- Do not use longer than one week unless directed by a doctor

Stop use and ask a doctor if conditions persist or gets worse.

Keep out of reach of children. In case of ingestion, get medical help or contact a Poison Control Center right away.

Directions

Clean the affected area.
Apply small amount of this product on the area 1-3 times daily.
Let the alcohol dry on skin before using bandages.
May be covered with a sterile bandage.

Other information

- Store at room temperature
- Does not contain, nor is intended as a substitute for grain or ethyl alcohol

Inactive ingredients

Water (Aqua)